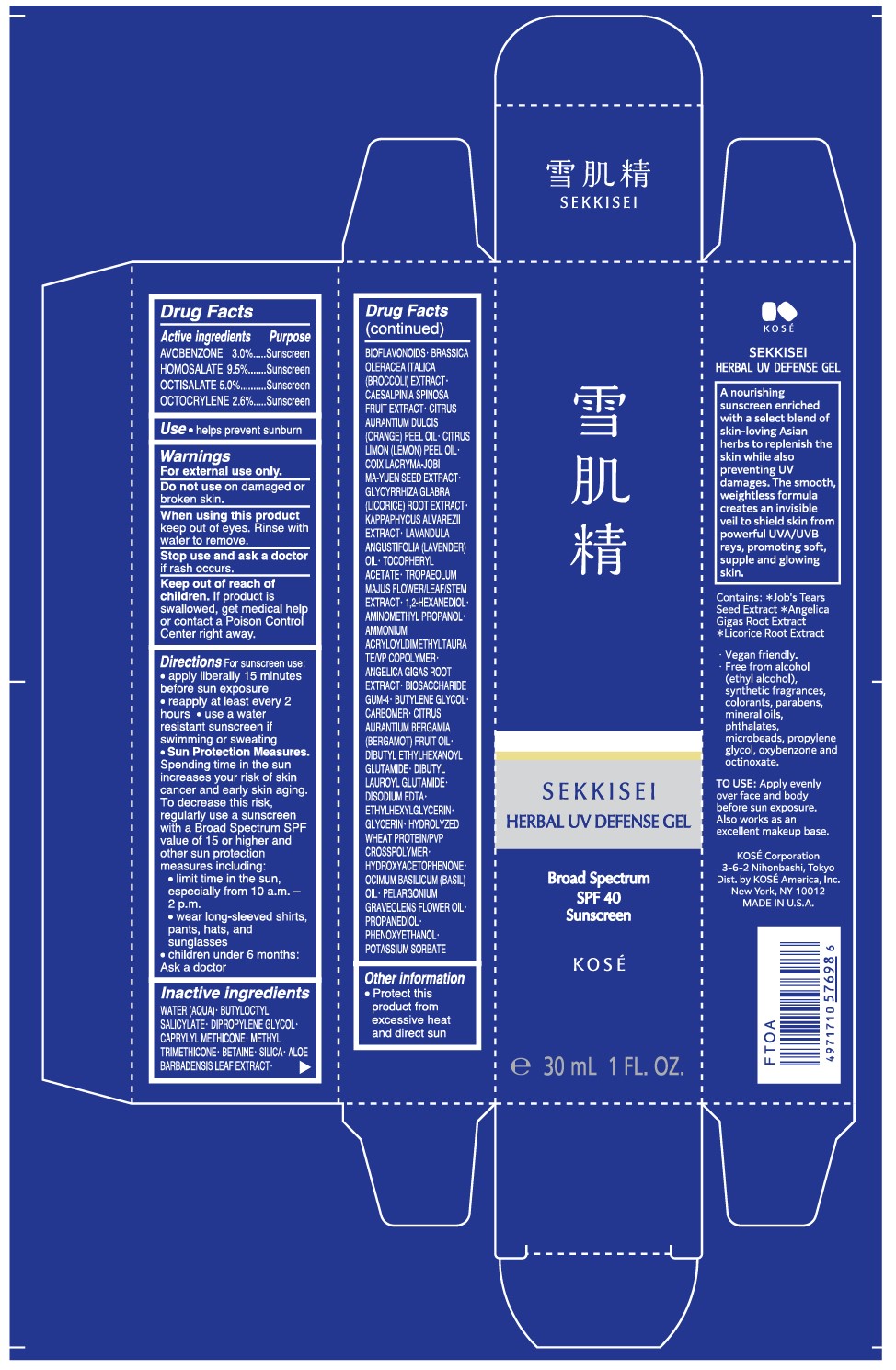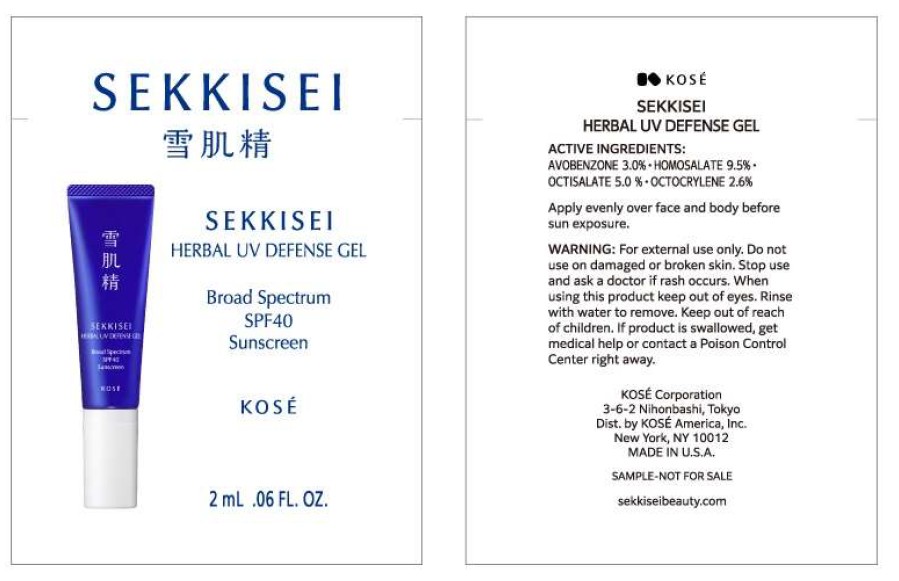 DRUG LABEL: SEKKISEI HERBAL UV DEFENSE gel
NDC: 66820-0400 | Form: GEL
Manufacturer: KOSÉ America, Inc.
Category: otc | Type: HUMAN OTC DRUG LABEL
Date: 20251031

ACTIVE INGREDIENTS: AVOBENZONE 30 mg/1 mL; HOMOSALATE 95 mg/1 mL; OCTISALATE 50 mg/1 mL; OCTOCRYLENE 26 mg/1 mL
INACTIVE INGREDIENTS: WATER; BUTYLOCTYL SALICYLATE; DIPROPYLENE GLYCOL; CAPRYLYL TRISILOXANE; METHYL TRIMETHICONE; BETAINE; SILICON DIOXIDE; ALOE VERA LEAF; CITRUS BIOFLAVONOIDS; BROCCOLI; CAESALPINIA SPINOSA FRUIT POD; ORANGE OIL, COLD PRESSED; LEMON OIL, COLD PRESSED; COIX LACRYMA-JOBI VAR. MA-YUEN SEED; GLYCYRRHIZA GLABRA; KAPPAPHYCUS ALVAREZII; LAVENDER OIL; .ALPHA.-TOCOPHEROL ACETATE; TROPAEOLUM MAJUS FLOWERING TOP; 1,2-HEXANEDIOL; AMINOMETHYLPROPANOL; AMMONIUM ACRYLOYLDIMETHYLTAURATE/VP COPOLYMER; ANGELICA GIGAS ROOT; BIOSACCHARIDE GUM-4; BUTYLENE GLYCOL; CARBOMER HOMOPOLYMER TYPE B (ALLYL PENTAERYTHRITOL OR ALLYL SUCROSE CROSSLINKED); BERGAMOT OIL; DIBUTYL ETHYLHEXANOYL GLUTAMIDE; DIBUTYL LAUROYL GLUTAMIDE; EDETATE DISODIUM; ETHYLHEXYLGLYCERIN; GLYCERIN; HYDROLYZED WHEAT PROTEIN (ENZYMATIC; 3000 MW); HYDROXYACETOPHENONE; BASIL OIL; PELARGONIUM GRAVEOLENS FLOWER OIL; PROPANEDIOL; PHENOXYETHANOL; POTASSIUM SORBATE

SEKKISEI HERBAL UV DEFENSE GEL BROAD SPECTRUM SPF 40 SUNSCREEN

Drug Facts

ACTIVE INGREDIENT

Avobenzone 3.0%

Homosalate 9.5%

Octisalate 5.0%

Octocrylene 2.6%

PURPOSE

Sunscreen

USES

- Helps Prevent Sunburn.

TO USE:Apply evenly over face and body before sun exposure. Also works as an excellent makeup base.

WARNINGS

For external use only.

Do not useon damaged or broken skin.

WHEN USING

When using this productkeep out of eyes. Rinse with water to remove.

Stop use and ask a doctorif rash occurs.

Keep out of reach of children. If product is swallowed, get medical help or contact a Poison Control Center right away.

DIRECTIONS

For sunscreen use:
• apply liberally 15 minutes before sun exposure
• reapply at least every 2 hours
• use a water resistant sunscreen if swimming or sweating
• Sun Protection Measures.
Spending time in the sun increases your risk of skin cancer and early skin aging. To decrease this risk, regularly use a sunscreen with a Broad Spectrum SPF value of 15 or higher and other sun protection measures including:
• limit time in the sun, especially from 10 a.m. - 2 p.m.
• wear long-sleeved shirts, pants, hats, and sunglasses
• children under 6 months: Ask a doctor

INACTIVE INGREDIENT

Water (AQUA), Butyloctyl Salicylate, Dipropylene Glycol, Caprylyl Methicone, Methyl Trimethicone, Betaine, Silica, Aloe Barbadensis Leaf Extract, Bioflavonoids, Brassica Oleracea Italica (Broccoli) Extract, Caesalpinia Spinosa Fruit Extract, Citrus Aurantium Dulcis (Orange) Peel Oil, Citrus Limon (Lemon) Peel Oil, Coix Lacryma-Jobi MA-YUEN Seed Extract, Glycyrrhiza Glabra (Licorice) Root Extract, Kappaphycus Alvarezii Extract, Lavandula Angustifolia (Lavender) Oil, Tocopheryl Acetate, Tropaeolum Majus Flower/Leaf/Stem Extract, 1,2-Hexanediol, Aminomethyl Propanol, Ammonium Acryloyldimethyltaura TE/VP Copolymer, Angelica Gigas Root Extract, Biosaccharide Gum-4, Butylene Glycol, Carbomer, Citrus Aurantium Bergamia (Bergamot) Fruit Oil, Dibutyl Ethylhexanoyl Glutamide, Dibutyl Lauroyl Glutamide, Disodium EDTA, Ethylhexylglycerin, Glycerin, Hydrolyzed Wheat Protein/PVP Crosspolymer, Hydroxyacetophenone, Ocimum Basilicum (Basil) Oil, Pelargonium Graveolens Flower Oil, Propanediol, Phenoxyethanol, Potassium Sorbate

Other information

Protect this product from excessive heat and direct sun

PRINCIPAL DISPLAY PANEL - 30 mL Tube

SEKKISEI HERBAL UV DEFENSE GEL

Broad Spectrum SPF 40 Sunscreen

KOSE

e 30 mL 1 FL. OZ.

Package Label Principal Display Panel

SEKKISEI

SEKKISEI

HERBAL UV DEFENSE GEL

Broad Spectrum

SPF40

Sunscreen

Kose

2 mL.06 FL. OZ.